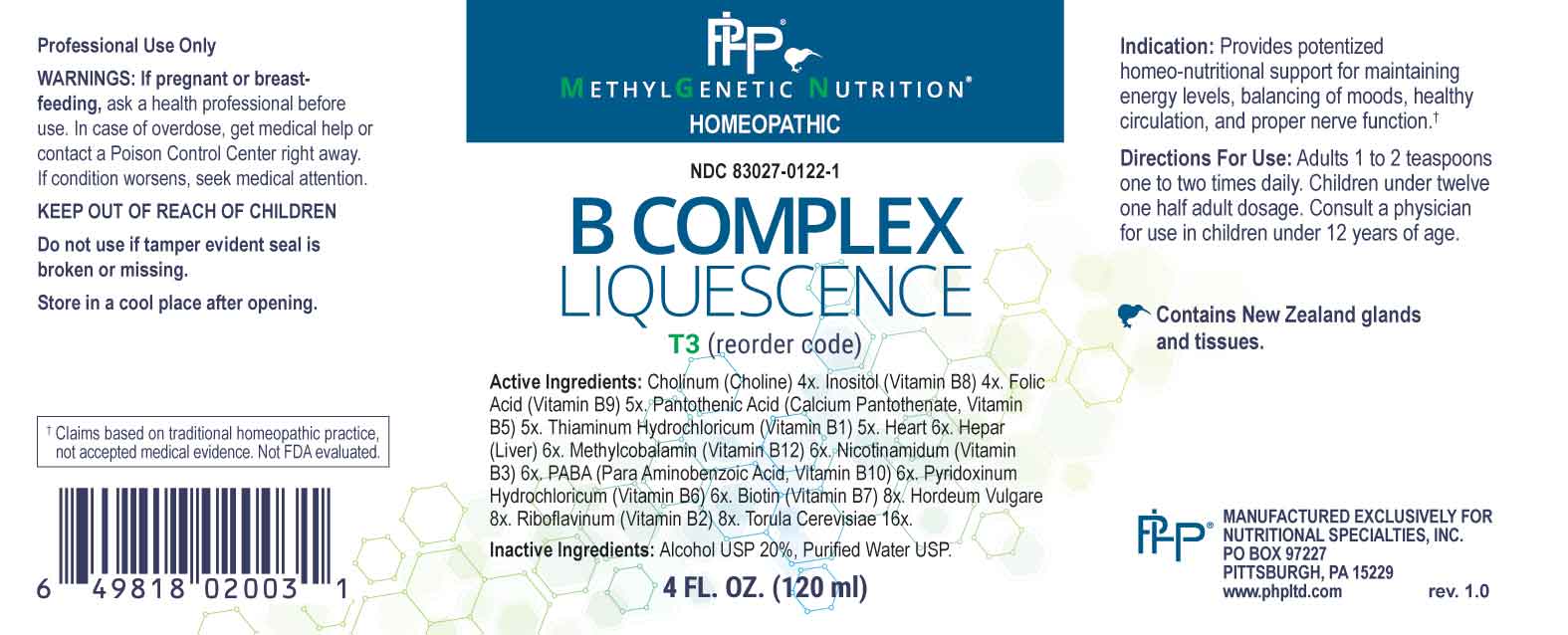 DRUG LABEL: B Complex Liquescence
NDC: 83027-0122 | Form: LIQUID
Manufacturer: Nutritional Specialties, Inc.
Category: homeopathic | Type: HUMAN OTC DRUG LABEL
Date: 20231009

ACTIVE INGREDIENTS: CHOLINE HYDROXIDE 4 [hp_X]/1 mL; INOSITOL 4 [hp_X]/1 mL; FOLIC ACID 5 [hp_X]/1 mL; CALCIUM PANTOTHENATE 5 [hp_X]/1 mL; THIAMINE HYDROCHLORIDE 5 [hp_X]/1 mL; BEEF HEART 6 [hp_X]/1 mL; BEEF LIVER 6 [hp_X]/1 mL; METHYLCOBALAMIN 6 [hp_X]/1 mL; NIACINAMIDE 6 [hp_X]/1 mL; AMINOBENZOIC ACID 6 [hp_X]/1 mL; PYRIDOXINE HYDROCHLORIDE 6 [hp_X]/1 mL; BIOTIN 8 [hp_X]/1 mL; HORDEUM VULGARE TOP 8 [hp_X]/1 mL; RIBOFLAVIN 8 [hp_X]/1 mL; SACCHAROMYCES CEREVISIAE 16 [hp_X]/1 mL
INACTIVE INGREDIENTS: WATER; ALCOHOL

DRUG FACTS:

ACTIVE INGREDIENTS:

Cholinum (Choline) 4X, Inositol (Vitamin B8) 4X, Folic Acid (Vitamin B9) 5X, Pantothenic Acid (Calcium Pantothenate, Vitamin B5) 5X, Thiaminum Hydrochloricum (Vitamin B1) 5X, Heart 6X, Hepar (Liver) 6X, Methylcobalamin (Vitamin B12) 6X, Nicotinamidum (Vitamin B3) 6X, PABA (Para Aminobenzoic Acid Vitamin B10) 6X, Pyridoxinum Hydrochloricum (Vitamin B6) 6X, Biotin (Vitamin B7) 8X, Hordeum Vulgare 8X, Riboflavinum (Vitamin B2) 8X, Torula Cerevisiae 16X.

PURPOSE:

Provides potentized homeo-nutritional support for maintaining energy levels, balancing of moods, healthy circulation, and proper nerve function.†

†Claims based on traditional homeopathic practice, not accepted medical evidence. Not FDA evaluated.

WARNINGS:

Professional Use Only

If pregnant or breast-feeding, ask a health professional before use.

In case of overdose, get medical help or contact a Poison Control Center right away.

If condition worsens, seek medical attention.

KEEP OUT OF REACH OF CHILDREN

Do not use if tamper evident seal is broken or missing.

Store in a cool place after opening

KEEP OUT OF REACH OF CHILDREN:

In case of overdose, get medical help or contact a Poison Control Center right away.

DIRECTIONS:

Adults 1 to 2 teaspoons one to two times daily. Children under twelve one half adult dosage. Consult a physician for use in children under 12 years of age.

INDICATIONS:

Provides potentized homeo-nutritional support for maintaining energy levels, balancing of moods, healthy circulation, and proper nerve function.†

†Claims based on traditional homeopathic practice, not accepted medical evidence. Not FDA evaluated.

INACTIVE INGREDIENTS:

Alcohol USP 20%, Purified Water USP.

QUESTIONS:

MANUFACTURED EXCLUSIVELY FOR

NUTRITIONAL SPECIALTIES, INC.

PO BOX 97227

PITTSBURG, PA 15229

www.phpltd.com

PACKAGE LABEL DISPLAY:

METHYLGENETIC NUTRITION

HOMEOPATHIC

NDC 83027-0122-1

B COMPLEX

LIQUESCENCE

4 FL. OZ (120 ml)